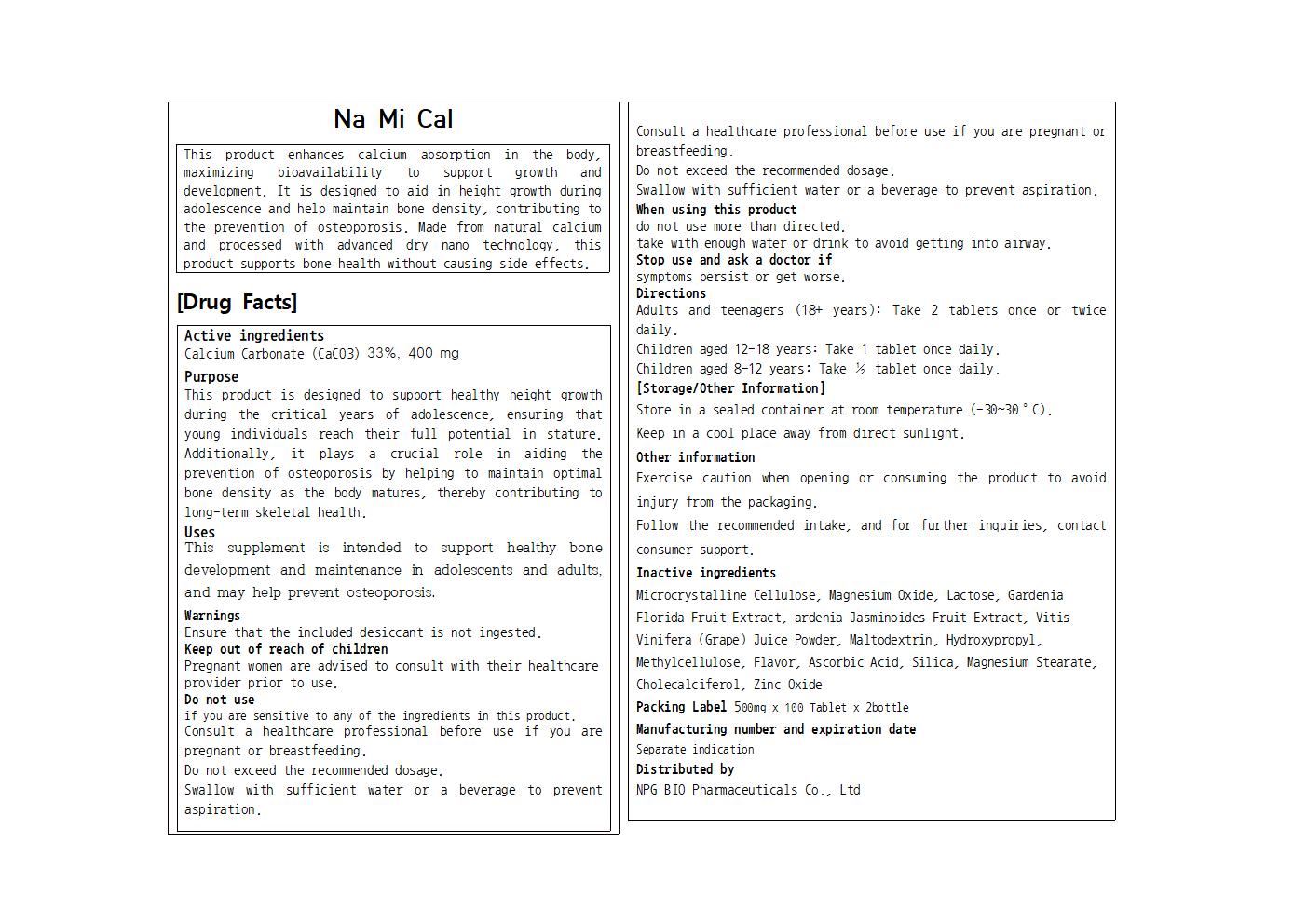 DRUG LABEL: Na Mi Cal
NDC: 84540-422 | Form: TABLET
Manufacturer: NPG Bio Pharmaceuticals Co.,Ltd.
Category: otc | Type: HUMAN OTC DRUG LABEL
Date: 20250827

ACTIVE INGREDIENTS: CALCIUM CARBONATE 200.4 mg/600 mg
INACTIVE INGREDIENTS: LACTOSE, UNSPECIFIED FORM; WINE GRAPE JUICE; ASCORBIC ACID; MICROCRYSTALLINE CELLULOSE; MAGNESIUM STEARATE; MALTODEXTRIN; HYDROXYPROPYL CELLULOSE, UNSPECIFIED; MAGNESIUM OXIDE; CHOLECALCIFEROL; SILICON DIOXIDE; ZINC OXIDE; GARDENIA JASMINOIDES FRUIT; METHYLCELLULOSE, UNSPECIFIED

84540-422 Na Mi Cal PTP

Active Ingredients

Calcium Carbonate (CaCO3) 33%, 400 mg

Purposes

This product is designed to support healthy height growth during the critical years of adolescence, ensuring that young individuals reach their full potential in stature. Additionally, it plays a crucial role in aiding the prevention of osteoporosis by helping to maintain optimal bone density as the body matures, thereby contributing to long-term skeletal health.

Uses

This supplement is intended to support healthy bone development and maintenance in adolescents and adults, and may help prevent osteoporosis.

Warnings

Ensure that the included desiccant is not ingested.

Warnings

Pregnant women are advised to consult with their healthcare provider prior to use.

Warnings

Stop use and ask a doctor if

symptoms persist or get worse.

Warnings

When using this product

do not use more than directed.

take with enough water or drink to avoid getting into airway.

Warnings

Ensure that the included desiccant is not ingested.

Inactive Ingredients

Microcrystalline Cellulose, Magnesium Oxide, Lactose, Gardenia Florida Fruit Extract, ardenia Jasminoides Fruit Extract, Vitis Vinifera (Grape) Juice Powder, Maltodextrin, Hydroxypropyl, Methylcellulose, Flavor, Ascorbic Acid, Silica, Magnesium Stearate, Cholecalciferol, Zinc Oxide

Direction

Adults and teenagers (18+ years): Take 2 tablets once or twice daily.

Children aged 12-18 years: Take 1 tablet once daily.

Children aged 8-12 years: Take ½ tablet once daily.

Label

NA MI CAL